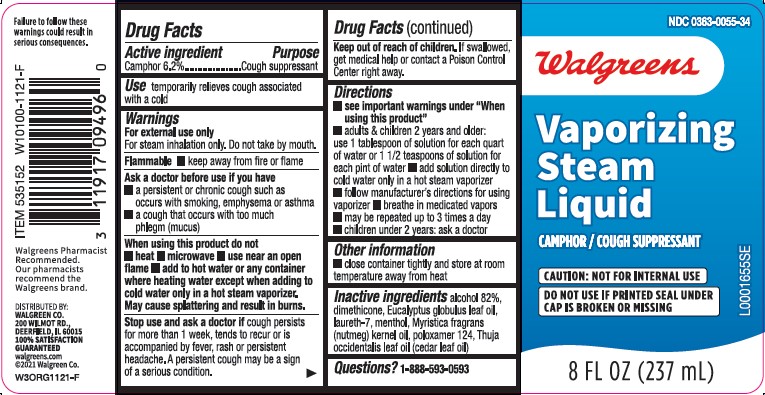 DRUG LABEL: Vaporizing
NDC: 0363-0055 | Form: INHALANT
Manufacturer: Walgreen Co.
Category: otc | Type: HUMAN OTC DRUG LABEL
Date: 20260212

ACTIVE INGREDIENTS: CAMPHOR (SYNTHETIC) 62 mg/1 mL
INACTIVE INGREDIENTS: ALCOHOL; DIMETHICONE; EUCALYPTUS OIL; LAURETH-7; MENTHOL; NUTMEG OIL; POLOXAMER 124; CEDAR LEAF OIL

Walgreens 397.002-397AA rev 2-AB
Medicated Vaporizing Steam Liquid

Safety information

Failure to follow these warnings could result in serious consequences.

Active Ingredient

Camphor 6.2%

Purpose

Cough suppressant

Use

temporarily relieves cough associated with a cold

Warnings

For external use only

For steam inhalation only. Do not take by mouth.

Flammable

- keep away from fire or flame.

Ask a doctor before use if you have

- a persistent or chronic cough such as occurs with smoking, emphsema or asthma
- a cough that occurs with too much phlegm (mucus)

When using this product do not

- heat
- microwave
- use near an open flame
- add to hot water or any container where heating water except when adding to cold water only in a hot steam vaporizer.

May cause splattering and result in burns.

Stop use and ask a doctor

if cough persists for more than 1 week, tends to recur or is accompanied by fever, rash, or persistent headache. A persistent cough may be a sign of a serious condition.

Keep out of reach of children

If swallowed, get medical or contact a Poison Control Center right away.

Directions

- see important warnings under "When using this product"
- adults & children 2 years and older: use 1 tablespoon of solution for each quart of water or 1 1/2 teaspoons of solution for each pint of water
- add solution directly to cold water only in a hot steam vaporizer
- follow manufacturer's directions for using vaporizer
- breath in medicated vapors
- may be repeated up to 3 times a day
- children under 2 years: ask a doctor

Other information

- close container tightly and store at room temperature away from heat

Inactive ingredients

alcohol 82%, dimethicone, Eucalyptus globulus leaf oil, laureth-7, menthol, Myristica fragrans (nutmeg) kernel oil, poloxamer 124, Thuja occidentalis leaf oil (cedar leaf oil)

Questions?

1-888-593-0593

ADVERSE REACTION

Walgreens Pharmacist Recommended.

Our Pharmacists recommend the Walgreens brand.

DISTRIBUTED BY: WALGREEN CO.

200 WILMOT RD., DEERFIELD, IL 60015

100% SATISACTION GUARANTEED

walgreens.com

2021 Walgreen Co.

principal display panel

NDC 0363-0055-34

Walgreens

Vaporizing

Steam

Liquid

CAMPHOR/COUGH SUPPRESSANT

CAUTION: NOT FOR INTERNAL USE.

DO NOT USE IF PRINTED SEAL UNDER CAP IS BROKEN OR MISSING

8 FL OZ (237 mL)